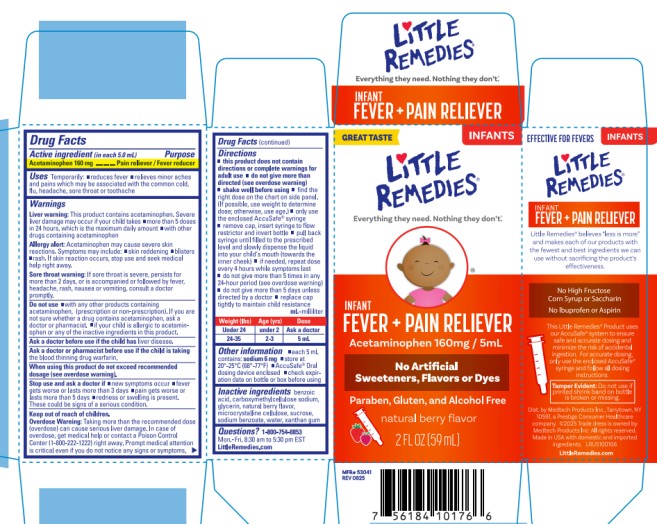 DRUG LABEL: Little Remedies Infant Fever/Pain Reliever
NDC: 63029-610 | Form: LIQUID
Manufacturer: Medtech Products Inc.
Category: otc | Type: HUMAN OTC DRUG LABEL
Date: 20251023

ACTIVE INGREDIENTS: ACETAMINOPHEN 160 mg/5 mL
INACTIVE INGREDIENTS: BENZOIC ACID; CARBOXYMETHYLCELLULOSE; GLYCERIN; MICROCRYSTALLINE CELLULOSE; SUCROSE; SODIUM BENZOATE; WATER; XANTHAN GUM

LITTLE REMEDIES INFANT FEVER PAIN RELIEVER - Berry

Drug Facts

Active ingredient

(in each 5 mL)

Acetaminophen 160 mg

Purpose

Pain Reliever/Fever Reducer

Uses

Temporarily:

- reduces fever
- relieves minor aches and pains which may be associated with the common cold, flu, headache, sore throat or toothache

Warnings

Liver warning: This product contains acetaminophen. Severe liver damage may occur if your child takes

- more than 5 doses in 24 hours, which is the maximum daily amount
- with other drugs containing acetaminophen.

Allergy Alert: Acetaminophen may cause severe skin reactions. Symptoms may include:

- skin reddening
- blisters
- rash.

If skin reaction occurs, stop use and seek medical help right away.

Sore Throat Warning: If sore throat is severe, persists for more than 2 days, or is accompanied or followed by fever, headache, rash, nausea or vomiting, consult a doctor promptly.

Do not use:

- with any other products containing acetaminophen (prescription or non-prescription). If you are not sure whether a drug contains acetaminophen, ask a doctor or pharmacist.
- If your child is allergic to acetaminophen or any of the inactive ingredients in this product.

Ask a doctor before use if

your child has liver disease.

Ask a doctor or pharmacist before use if

your child is taking the blood thinning drug warfarin.

When using this product

do not exceed recommended dosage (see overdose warning.)

Stop use and ask a doctor if

- new symptoms occur
- fever gets worse or lasts more than 3 days
- pain gets worse or lasts more than 5 days
- redness or swelling is present. These could be signs of a serious condition.

Keep out of reach of children.

Overdose Warning: Taking more than the recommended dose (overdose) can cause serious liver damage. In case of overdose, get medical help or contact a Poison Control Center (1-800-222-1222) immediately. Prompt medical attention is critical even if you do not notice any signs or symptoms.

Directions

- this product does not contain directions or complete warnings for adult use
- do not give more than directed (see overdose warning)
- shake well before using

- find the right dose on the chart below. (If possible, use weight to determine dose; otherwise, use age.)
- only use the enclosed AccuSafe®syringe
- remove cap, insert syringe to flow restrictor and invert bottle
- pull back syringe until filled to prescribed level and slowly dispense the liquid into your child’s mouth (toward the inner cheek)
- if needed, repeat dose every 4 hours while symptoms last
- do not give more than 5 times in any 24-hour period (see overdose warning)
- do not give more than 5 days unless directed by a doctor
- replace cap tightly to maintain child resistance

mL=mililiter

Weight (lbs) | Age (yrs) | Dose
Under 24 | Under 2 | Ask a doctor
24-35 | 2-3 | 5 mL

Other information

- each 5 mL contains: sodium 6 mg
- store at 20-25ºC (68-77ºF)
- AccuSafe® Oral dosing device enclosed
- check expiration date on bottle or box before using

Inactive ingredients

benzoic acid, carboxymethlcellulose, glycerin, natural berry flavor, microcrystalline cellulose, sucrose, sodium benzoate, water, xanthan gum

Questions?

1-800-54-8853 Mon. – Fri. 8:00 a.m.to 8:00 p.m. EST

LittleRemedies.com

PRINCIPAL DISPLAY PANEL

Little Remedies®
INFANT

FEVER+PAIN RELIEVER
Acetaminophen 160 mg / 5 mL

natural berry flavor
2 FL OZ (59 mL)